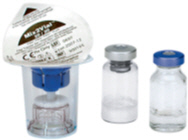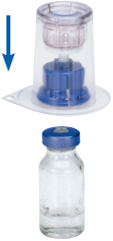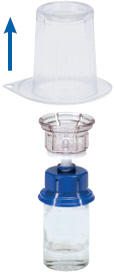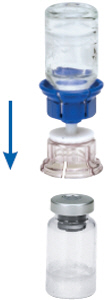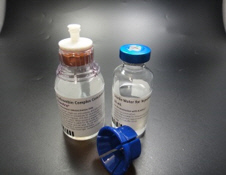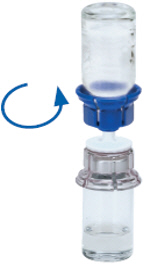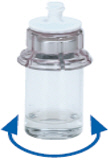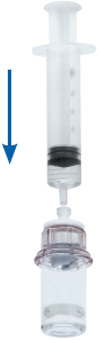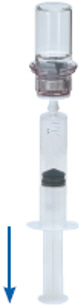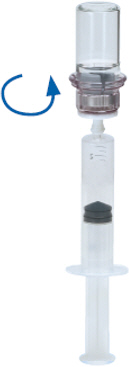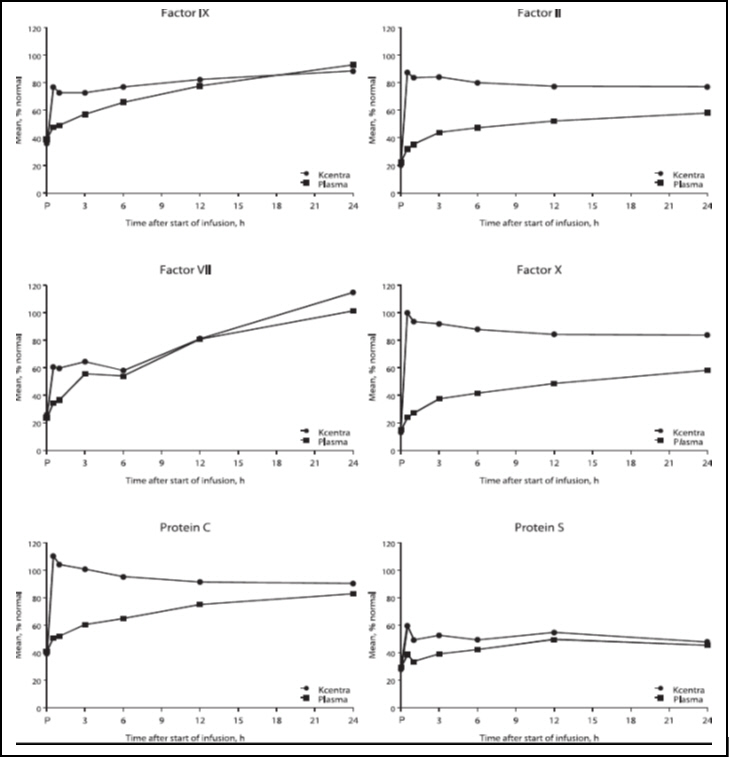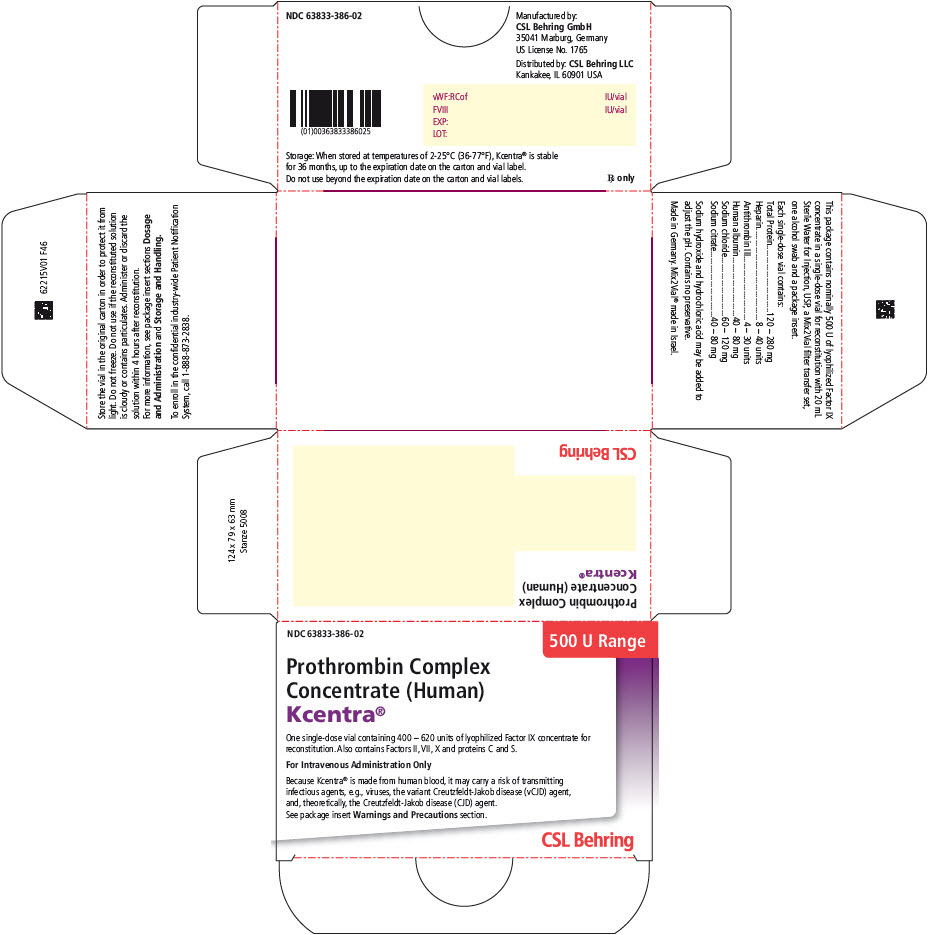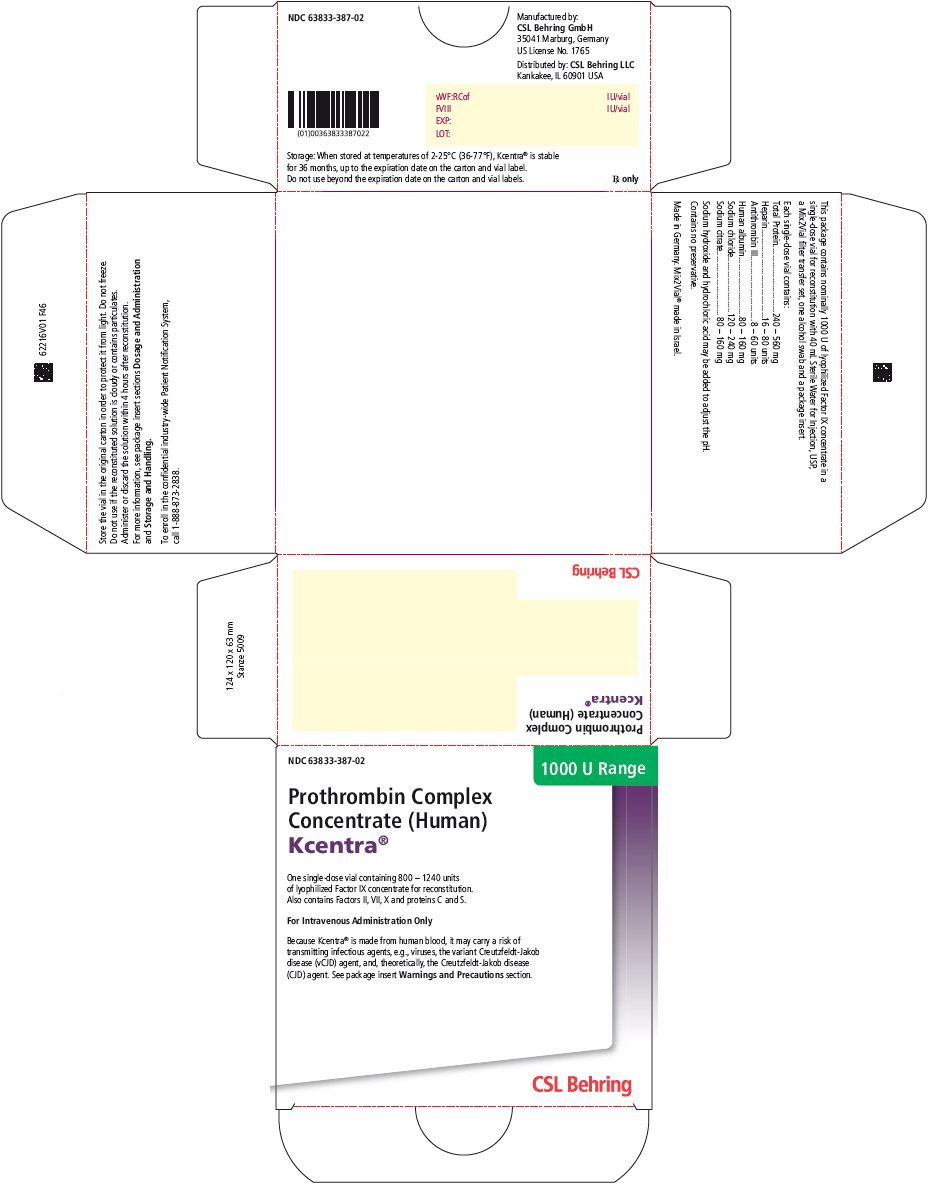 DRUG LABEL: Kcentra
NDC: 63833-386 | Form: KIT | Route: INTRAVENOUS
Manufacturer: CSL Behring GmbH
Category: other | Type: PLASMA DERIVATIVE
Date: 20230516

ACTIVE INGREDIENTS: PROTHROMBIN 590 U/20 mL; COAGULATION FACTOR VII HUMAN 350 U/20 mL; COAGULATION FACTOR IX HUMAN 510 U/20 mL; COAGULATION FACTOR X HUMAN 760 U/20 mL; Protein C 620 U/20 mL; Protein S Human 460 U/20 mL
INACTIVE INGREDIENTS: Heparin 24 U/20 mL; Antithrombin III Human 17 U/20 mL; Albumin Human 60 U/20 mL; Sodium chloride 90 U/20 mL; Sodium citrate, unspecified form 60 U/20 mL; Hydrochloric acid; Sodium hydroxide; Water

HIGHLIGHTS OF PRESCRIBING INFORMATION

These highlights do not include all the information needed to use KCENTRA safely and effectively. See full prescribing information for KCENTRA.
KCENTRA (Prothrombin Complex Concentrate (Human))
For Intravenous Use, Lyophilized Powder for Reconstitution
Initial U.S. Approval: 2013

WARNING: ARTERIAL AND VENOUS THROMBOEMBOLIC COMPLICATIONS

Patients being treated with Vitamin K antagonists (VKA) therapy have underlying disease states that predispose them to thromboembolic events. Potential benefits of reversing VKA should be weighed against the potential risks of thromboembolic events, especially in patients with the history of a thromboembolic event. Resumption of anticoagulation should be carefully considered as soon as the risk of thromboembolic events outweighs the risk of acute bleeding.

- Both fatal and non-fatal arterial and venous thromboembolic complications have been reported with Kcentra in clinical trials and post marketing surveillance. Monitor patients receiving KCENTRA for signs and symptoms of thromboembolic events.
- KCENTRA was not studied in subjects who had a thromboembolic event, myocardial infarction, disseminated intravascular coagulation, cerebral vascular accident, transient ischemic attack, unstable angina pectoris, or severe peripheral vascular disease within the prior 3 months. KCENTRA may not be suitable in patients with thromboembolic events in the prior 3 months. (5.2)

RECENT MAJOR CHANGES

Warnings and Precautions (5.2) | 05/2023

1 INDICATIONS AND USAGE

KCENTRA, Prothrombin Complex Concentrate (Human), is a blood coagulation factor replacement product indicated for the urgent reversal of acquired coagulation factor deficiency induced by Vitamin K antagonist (VKA, e.g., warfarin) therapy in adult patients with:

- acute major bleeding or
- need for an urgent surgery/invasive procedure. (1)

2 DOSAGE AND ADMINISTRATION

For intravenous use after reconstitution only.

- KCENTRA dosing should be individualized based on the patient's baseline International Normalized Ratio (INR) value, and body weight. (2.1)
- Administer Vitamin K concurrently to patients receiving KCENTRA to maintain factor levels once the effects of KCENTRA have diminished.
- The safety and effectiveness of repeat dosing have not been established and it is not recommended. (2.1)
- Administer reconstituted KCENTRA at a rate of 0.12 mL/kg/min (~3 units/kg/min) up to a maximum rate of 8.4 mL/min (~210 units/min). (2.3)

Pre-treatment INR | 2–< 4 | 4–6 | > 6
Dose [Dosing is based on body weight. Dose based on actual potency is stated on the vial, which will vary from 20--31 Factor IX units/mL after reconstitution. The actual potency for 500 unit vial ranges from 400-620 units/vial. The actual potency for 1000 unit vial ranges from 800-1240 units/vial.] of KCENTRA (units [Units refer to International Units.] of Factor IX) / kg body weight | 25 | 35 | 50
Maximum dose [Dose is based on body weight up to but not exceeding 100 kg. For patients weighing more than 100 kg, maximum dose should not be exceeded.] (units of Factor IX) | Not to exceed 2500 | Not to exceed 3500 | Not to exceed 5000

3 DOSAGE FORMS AND STRENGTHS

KCENTRA is available as a white or slightly colored lyophilized concentrate in a single-dose vial containing coagulation Factors II, VII, IX and X, and antithrombotic Proteins C and S. (3)

4 CONTRAINDICATIONS

KCENTRA is contraindicated in patients with:

- Known anaphylactic or severe systemic reactions to KCENTRA or any components in KCENTRA including heparin, Factors II, VII, IX, X, Proteins C and S, Antithrombin III and human albumin. (4)
- Disseminated intravascular coagulation. (4)
- Known heparin-induced thrombocytopenia. KCENTRA contains heparin. (4)

5 WARNINGS AND PRECAUTIONS

- Hypersensitivity reactions may occur. If necessary, discontinue administration and institute appropriate treatment. (5.1)
- Arterial and venous thromboembolic complications have been reported in patients receiving KCENTRA. Monitor patients receiving KCENTRA for signs and symptoms of thromboembolic events. KCENTRA was not studied in subjects who had a thrombotic or thromboembolic (TE) event within the prior 3 months. KCENTRA may not be suitable in patients with thromboembolic events in the prior 3 months. (5.2)
- KCENTRA is made from human blood and may carry a risk of transmitting infectious agents, e.g., viruses, the variant Creutzfeldt-Jakob disease (vCJD) agent, and theoretically, the Creutzfeldt-Jakob disease (CJD) agent. (5.3)

6 ADVERSE REACTIONS

- The most common adverse reactions (ARs) (frequency ≥ 2.8%) observed in subjects receiving KCENTRA were headache, nausea/vomiting, hypotension, and anemia. (6)
- The most serious ARs were thromboembolic events including stroke, pulmonary embolism, and deep vein thrombosis. (6)

To report SUSPECTED ADVERSE REACTIONS, contact CSL Behring at 1-866-915-6958 or FDA at 1-800-FDA-1088 or www.fda.gov/medwatch.

FULL PRESCRIBING INFORMATION

WARNING: ARTERIAL AND VENOUS THROMBOEMBOLIC COMPLICATIONS

Patients being treated with Vitamin K antagonists (VKA) therapy have underlying disease states that predispose them to thromboembolic events. Potential benefits of reversing VKA should be weighed against the potential risks of thromboembolic events (TE), especially in patients with the history of a thromboembolic event. Resumption of anticoagulation should be carefully considered as soon as the risk of thromboembolic events outweighs the risk of acute bleeding.

- Both fatal and non-fatal arterial and venous thromboembolic complications have been reported with KCENTRA in clinical trials and post marketing surveillance. Monitor patients receiving KCENTRA for signs and symptoms of thromboembolic events. (5.2)
- KCENTRA was not studied in subjects who had a thromboembolic event, myocardial infarction, disseminated intravascular coagulation, cerebral vascular accident, transient ischemic attack, unstable angina pectoris, or severe peripheral vascular disease within the prior 3 months. KCENTRA may not be suitable in patients with thromboembolic events in the prior 3 months. (5.2)

1 INDICATIONS AND USAGE

KCENTRA, (Prothrombin Complex Concentrate (Human)), is a blood coagulation factor replacement product indicated for the urgent reversal of acquired coagulation factor deficiency induced by Vitamin K antagonist (VKA, e.g., warfarin) therapy in adult patients with:

- acute major bleeding or
- need for an urgent surgery/invasive procedure.

2 DOSAGE AND ADMINISTRATION

For intravenous use after reconstitution only.

2.1 Dosage

- Measurement of INR prior to treatment and close to the time of dosing is important because coagulation factors may be unstable in patients with acute major bleeding or an urgent need for surgery and other invasive procedures.
- Individualize KCENTRA dosing based on the patient's current pre-dose International Normalized Ratio (INR) value, and body weight (see Table 1).
- The actual potency per vial of Factors II, VII, IX and X, Proteins C and S is stated on the carton.
- Administer Vitamin K concurrently to patients receiving KCENTRA. Vitamin K is administered to maintain Vitamin K-dependent clotting factor levels once the effects of KCENTRA have diminished.
- The safety and effectiveness of repeat dosing have not been established and it is not recommended.
- Dose ranging within pre-treatment INR groups has not been studied in randomized clinical trials of KCENTRA.

Table 1: Dosage Required for Reversal of VKA Anticoagulation in Patients with acute major bleeding or need for an urgent surgery/invasive procedure
Pre-treatment INR | 2–< 4 | 4–6 | > 6
Dose [Dosing is based on body weight. Dose based on actual potency is stated on the vial, which will vary from 20–31 Factor IX units/mL after reconstitution. The actual potency for 500 unit vial ranges from 400-620 units/vial. The actual potency for 1000 unit vial ranges from 800-1240 units/vial.] of KCENTRA (units [Units refer to International Units.] of Factor IX) / kg body weight | 25 | 35 | 50
Maximum dose [Dose is based on body weight up to but not exceeding 100 kg. For patients weighing more than 100 kg, maximum dose should not be exceeded.] (units of Factor IX) | Not to exceed 2500 | Not to exceed 3500 | Not to exceed 5000

Example dosing calculation for 80 kg patient

For example, an 80 kg patient with a baseline of INR of 5.0, the dose would be 2,800 Factor IX units of KCENTRA, calculated as follows based on INR range of 4–6, see Table 1:

35 units of Factor IX/kg × 80 kg = 2,800 units of Factor IX required [For a vial with an actual potency of 30 units/mL Factor IX, 93 mL would be given (2,800 U/30 U per mL = 93 mL).]

Monitor INR and clinical response during and after treatment. In clinical trials, KCENTRA decreased the INR to ≤ 1.3 within 30 minutes in most subjects. The relationship between this or other INR values and clinical hemostasis in patients has not been established [see Clinical Studies (14)].

2.2 Preparation and Reconstitution

- Reconstitute KCENTRA using aseptic technique with 20 mL (nominal potency 500 U kit) or 40 mL (nominal potency 1000 U kit) of Sterile Water for Injection (diluent) provided in the kit.
- Do not use KCENTRA beyond the expiration date on the vial label and carton.
- KCENTRA is for single-dose only. Contains no preservatives. Discard partially used vials.

Kcentra Reconstitution Instructions

1. Ensure that the KCENTRA vial and diluent vial are at room temperature.
2. Remove flip caps from the KCENTRA and diluent vials.
3. Wipe the stoppers with the alcohol swab provided and allow to dry prior to opening the Mix2Vial package.
4. Open the Mix2Vial package by peeling off the lid (Fig. 1). Do not remove the Mix2Vial from the blister package.
  Fig. 1
5. Place the diluent vial on an even, clean surface and hold the vial tight. Take the Mix2Vial together with the blister package and push the spike of the blue adapter end straight down through the diluent vial stopper (Fig. 2).
  Fig. 2
6. Carefully remove the blister package from the Mix2Vial set by holding at the rim, and pulling vertically upwards. Make sure that you only pull away the blister package and not the Mix2Vial set (Fig. 3).
  Fig. 3
7. Place the KCENTRA vial on an even and firm surface. Invert the diluent vial with the Mix2Vial set attached and push the spike of the transparent adapter end straight down through the KCENTRA vial stopper (Fig. 4). The diluent will automatically flow into the KCENTRA vial.
  Fig. 4
  Note: If the vacuum in the KCENTRA vial is accidentally lost during reconstitution with the Mix2Vial device, the transfer with the Mix2Vial will not work.
  In this case, separate the set into two pieces as illustrated in Fig. 6 below; do not discard the diluent vial. Place the KCENTRA vial aside on a flat surface. Remove the blue adapter end from the diluent vial of the Mix2Vial set (Fig. 5) by lifting and bending the blue adapter to the side until it disconnects from the diluent vial.
  For reconstitution:
  - Using a separate sterile needle and syringe, withdraw the remaining diluent. Remove the needle from the syringe.
  - Attach the syringe to the transparent adapter of the KCENTRA vial as illustrated in Fig. 8 below, and transfer the entire diluent volume into the KCENTRA vial. Remove syringe.
  - Gently swirl the KCENTRA vial to ensure the product is fully dissolved. Do not shake.
  - Proceed to step 10.
  Fig. 5
8. With one hand, grasp the KCENTRA-side of the Mix2Vial set and with the other hand grasp the diluent-side and unscrew the set carefully counterclockwise into two pieces (Fig. 6). Discard the diluent vial with the blue Mix2Vial adapter attached.
  Fig. 6
9. Gently swirl the KCENTRA vial with the transparent adapter attached until the substance is fully dissolved (Fig. 7). Do not shake.
  Fig. 7
10. Draw air into an empty, sterile syringe. While the KCENTRA vial is upright, connect the syringe to the Mix2Vial's Luer Lock fitting by screwing clockwise. Inject air into the KCENTRA vial (Fig. 8).
  Fig. 8
11. While keeping the syringe plunger pressed, turn the system upside down and draw the solution into the syringe by pulling the plunger back slowly (Fig. 9).
  Fig. 9
12. Now that the solution has been transferred into the syringe, firmly hold on to the barrel of the syringe (keeping the syringe plunger facing down) and disconnect the transparent Mix2Vial adapter from the syringe by unscrewing counterclockwise (Fig. 10). Attach the syringe to a suitable intravenous administration set.
  Fig. 10
13. After reconstitution, administration should begin promptly or within 4 hours.
14. If the same patient is to receive more than one vial, you may pool the contents of multiple vials. Use a separate unused Mix2Vial transfer set for each product vial.

2.3 Administration

- Do not mix KCENTRA with other medicinal products; administer through a separate infusion line.
- Visually inspect the reconstituted solution for particulate matter and discoloration prior to administration whenever solution and container permit. Reconstituted KCENTRA solution should be colorless, clear to slightly opalescent, and free from visible particles. Do not use if the solution is cloudy, discolored, or contains particulates.
- Use aseptic technique when administering KCENTRA.
- Administer at room temperature.
- Administer by intravenous infusion at a rate of 0.12 mL/kg/min (~3 units/kg/min), up to a maximum rate of 8.4 mL/min (~210 units/min).
- No blood should enter the syringe, as there is a possibility of fibrin clot formation.

3 DOSAGE FORMS AND STRENGTHS

- KCENTRA is available as a white or slightly colored lyophilized concentrate in a single-dose vial containing coagulation Factors II, VII, IX and X, and antithrombotic Proteins C and S.
- KCENTRA potency (units) is defined by Factor IX content. The actual potency for 500 unit vial ranges from 400-620 Factor IX units/vial. The actual potency for 1000 unit vial ranges from 800-1240 Factor IX units/vial. The actual content of Factor IX as measured in units of potency for the vial before reconstitution is stated by the expiration date. When reconstituted, the final concentration of drug product in Factor IX units will be in a range from 20–31 units/mL.
- The actual units of potency for each coagulation factor (Factors II, VII, IX and X), and Proteins C and S are stated on the carton.

4 CONTRAINDICATIONS

KCENTRA is contraindicated in:

- Patients with known anaphylactic or severe systemic reactions to KCENTRA or any components in KCENTRA including heparin, Factors II, VII, IX, X, Proteins C and S, Antithrombin III and human albumin.
- Patients with disseminated intravascular coagulation (DIC).
- Patients with known heparin-induced thrombocytopenia (HIT). KCENTRA contains heparin [see Description (11)].

5 WARNINGS AND PRECAUTIONS

5.1 Hypersensitivity Reactions

Hypersensitivity reactions including flushing, urticaria, tachycardia, anxiety, angioedema, wheezing, nausea, vomiting, hypotension, tachypnea, dyspnea, pulmonary edema, and bronchospasm have been observed with KCENTRA.

If severe allergic reaction or anaphylactic type reactions occur, immediately discontinue administration, and institute appropriate treatment.

5.2 Thromboembolic Risk/Complications

Both fatal and non-fatal arterial thromboembolic events (including acute myocardial infarction and arterial thrombosis), and venous thromboembolic events (including pulmonary embolism and venous thrombosis) and disseminated intravascular coagulation have been reported with KCENTRA in clinical trials and post marketing surveillance [see Adverse Reactions (6) and Clinical Studies (14)]. Patients being treated with VKA therapy have underlying disease states that predispose them to thromboembolic events. Reversing VKA therapy exposes patients to the thromboembolic risk of their underlying disease. Resumption of anticoagulation should be carefully considered following administration of KCENTRA and Vitamin K once the risk of thromboembolic events outweighs the risk of bleeding.

Thromboembolic events occurred more frequently following KCENTRA compared to plasma in a randomized, plasma controlled trial in subjects requiring urgent reversal of VKA anticoagulation due to acute major bleeding, and the excess in thromboembolic events was more pronounced among subjects who had a history of prior thromboembolic event, although these differences were not statistically significant [see Adverse Reactions (6.1) and Clinical Studies (14)].

In a postmarketing observational study, there was no significant difference in the risk of post-treatment thromboembolic events after receiving KCENTRA compared with plasma therapy for VKA-associated acute major bleeding [see Adverse Reactions (6.2)].

Potential benefits of treatment with KCENTRA should be weighed against the potential risks of thromboembolic events [see Adverse Reactions (6)]. Patients with a history of thrombotic events, myocardial infarction, cerebral vascular accident, transient ischemic attack, unstable angina pectoris, severe peripheral vascular disease, or disseminated intravascular coagulation, within the previous 3 months were excluded from participating in the plasma-controlled RCT. KCENTRA may not be suitable in patients with thromboembolic events in the prior 3 months. Because of the risk of thromboembolism associated with reversal of VKA, closely monitor patients for signs and symptoms of thromboembolism during and after administration of KCENTRA [see 17 Patient Counseling Information].

5.3 Transmissible Infectious Agents

Because KCENTRA is made from human blood, it may carry a risk of transmitting infectious agents, e.g., viruses, the variant Creutzfeldt-Jakob disease (vCJD) agent, and, theoretically, the Creutzfeldt-Jakob disease (CJD) agent. There is also the possibility that unknown infectious agents may be present in such products. Despite the use of two dedicated virus reduction steps in manufacturing to reduce risks, such products may still potentially transmit disease.

Reports of suspected virus transmission of hepatitis A, B, C, and HIV were generally confounded by concomitant administration of blood/blood components and/or other plasma-derived products. No causal relationship to KCENTRA administration was established for any of these reports since introduction of a virus filtration step in 1996.

All infections thought by a physician to have been possibly transmitted by KCENTRA should be reported by the physician or other healthcare provider to the CSL Behring Pharmacovigilance Department at 1-866-915-6958 or FDA at 1-800-FDA-1088 or www.fda.gov/medwatch.

6 ADVERSE REACTIONS

The most common adverse reactions (ARs) (frequency ≥2.8%) observed in subjects receiving KCENTRA were headache, nausea/vomiting, hypotension, and anemia.

The most serious ARs were thromboembolic events including stroke, pulmonary embolism, and deep vein thrombosis.

The following serious adverse reactions are described below and/or elsewhere in the labeling:

- Hypersensitivity Reactions [see Warnings and Precautions (5.1)]
- Arterial and venous thromboembolic complications [see Boxed Warning and Warnings and Precautions (5.2)]
- Possible transmission of infectious agents [see Warnings and Precautions (5.3)]

6.1 Clinical Trials Experience

Because clinical studies are conducted under widely varying conditions, adverse reaction rates observed in the clinical trials of a drug cannot be directly compared to rates in the clinical trials of another drug and may not reflect the rates observed in practice.

Randomized, Plasma-Controlled Trial in Acute Major Bleeding

In a prospective, randomized, open-label, active-controlled multicenter non-inferiority trial, 212 subjects who required urgent reversal of VKA therapy due to acute major bleeding were enrolled and randomized to treatment; 103 were treated with KCENTRA and 109 with plasma. Subjects with a history of a thrombotic event, myocardial infarction, cerebral vascular accident, transient ischemic attack, unstable angina pectoris, severe peripheral vascular disease, or disseminated intravascular coagulation, within the previous 3 months were excluded from participating. Subjects ranged in age from 26 years to 96 years.

Randomized, Plasma-Controlled Trial in Urgent Surgery/Invasive Procedures

In a prospective, randomized, open-label, active-controlled, multicenter non-inferiority trial, 176 subjects who required urgent reversal of VKA therapy due to the need for an urgent surgical or urgent invasive procedure were enrolled; 88 were treated with KCENTRA and 88 with plasma. Subjects ranged in age from 27 years to 94 years.

Adverse reactions are summarized for KCENTRA and plasma in the Acute Major Bleeding and Urgent Surgery/Invasive Procedures RCTs (see Table 2).

Adverse Reactions are defined as adverse events that began during or within 72 hours of test product infusion plus adverse events considered possibly/probably related or related to study treatment according to the investigator, sponsor, or the blinded safety adjudication board (SAB), and with at least a 1.3‐fold difference between treatments.

Table 2: Adverse Reactions Reported in more than 5 Subjects (≥2.8%) Following KCENTRA or Plasma Administration in RCTs
 | No. (%) of subjects
 | KCENTRA (N = 191) | Plasma (N = 197)
Nervous system disorders
Headache | 14 (7.3%) | 7 (3.6%)
Respiratory, thoracic, and mediastinal disorders
Pleural effusion | 8 (4.2%) | 3 (1.5%)
Respiratory distress/dyspnea/hypoxia | 7 (3.7%) | 10 (5.1%)
Pulmonary edema | 3 (1.6%) | 10 (5.1%)
Gastrointestinal disorders
Nausea/vomiting | 12 (6.3%) | 8 (4.1%)
Diarrhea | 4 (2.1%) | 7 (3.6%)
Cardiac disorders
Tachycardia | 9 (4.7%) | 2 (1.0%)
Atrial fibrillation | 8 (4.2%) | 6 (3.0%)
Metabolism and nutrition disorders
Fluid overload [Includes fluid overload and cardiac failure congestive] | 5 (2.6%) | 16 (8.1%)
Hypokalemia | 9 (4.7%) | 14 (7.1%)
Psychiatric disorders
Insomnia | 9 (4.7%) | 6 (3.0%)
Vascular disorders
Hypotension [Includes orthostatic hypotension, hypotension, and hemorrhagic shock] | 14 (7.3%) | 10 (5.1%)
Injury, poisoning, and procedural complications
Skin laceration/contusion/subcutaneous hematoma | 8 (4.2%) | 5 (2.5%)
Blood and lymphatic disorders
Anemia [Includes anemia, hemoglobin decreased, and hematocrit decreased] | 11 (5.8%) | 16 (8.1%)

Serious adverse reactions in subjects receiving KCENTRA in both RCTs included ischemic cerebrovascular accident (stroke), DVT, thrombosis, and venous insufficiency. Serious adverse reactions in both RCTs for plasma included myocardial ischemia, myocardial infarction, fluid overload, embolic cerebral infarction, pulmonary edema, respiratory failure, and DVT.

There were a total of 10 subjects (9.7%) who died in the KCENTRA group (1 additional death occurred on day 46 just after completion of the study reporting period) and 5 (4.6%) who died in the plasma group in the plasma-controlled RCT in acute major bleeding. The 95% confidence interval for the KCENTRA minus plasma between-group difference in deaths ranged from -2.7% to 13.5%. From the plasma-controlled RCT in urgent surgery/invasive procedures, there were a total of 3 subjects (3.4%) who died in the KCENTRA group (1 additional death occurred on day 48 after completion of the study reporting period) and 8 (9.1%) who died in the plasma group. The 95% confidence interval for the KCENTRA minus plasma between-group difference in deaths in this trial ranged from -14.6% to 2.7%. One death in the KCENTRA group in the RCT in Acute Major Bleeding and one death in the plasma group in the RCT in urgent surgery/invasive procedures were considered possibly related to study treatment according to an assessment of masked data by an independent safety adjudication board. No factors common to all deaths were identified, except for the frequent findings of a high comorbidity burden, advanced age, and death after being placed on comfort care. Although, a greater proportion of subjects in the RCT in acute major bleeding than in the RCT in surgery/invasive procedure received the highest two recommended doses of KCENTRA because more subjects in the trial in acute major bleeding had a baseline INR in the ranges of 4–6 and > 6.0, an analysis of deaths and factor levels in subjects with major bleeding revealed that subjects who died had similar median factor levels to subjects that did not die. Additionally, outliers with supraphysiologic factor levels did not have a mortality rate out of proportion to the overall population.

Fluid Overload

There were 9 subjects (4.7%, all non-related by investigator assessment) in the KCENTRA group who experienced fluid overload in the plasma-controlled RCTs in acute major bleeding and urgent surgery/invasive procedures and 25 (12.7%, 13 events related by investigator assessment) who had fluid overload in the plasma group. The 95% confidence interval for the KCENTRA minus Plasma between-group difference in fluid overload event incidence ranged from -14.1% to -2.0%.

Subgroup analyses of the RCTs in acute major bleeding and urgent surgery/invasive procedures according to whether subjects with fluid overload events had a prior history of congestive heart failure are presented in Table 3.

Table 3: Subjects with Fluid Overload Events by Prior History of Congestive Heart Failure in RCTs
Subgroup | Acute Major Bleeding Study |  |  |  | Urgent Surgery/Invasive Procedures Study
Subgroup | KCENTRA |  | Plasma |  | KCENTRA |  | Plasma
Subgroup | N | Fluid Overload N (%) | N | Fluid Overload N (%) | N | Fluid Overload N (%) | N | Fluid Overload N (%)
All subjects | 103 | 6 (5.8) | 109 | 14 (12.8) | 88 | 3 (3.4) | 88 | 11 (12.5)
With history of CHF | 46 | 4 (8.7) | 44 | 11 (25.0) | 24 | 1 (4.2) | 36 | 6 (16.7)
Without history of CHF | 57 | 2 (3.5) | 65 | 3 (4.6) | 64 | 2 (3.1) | 52 | 5 (9.6)

Thromboembolic Events

In RCTs, there were 13 subjects (6.8%) in the KCENTRA group who experienced possible thromboembolic events (TEEs) and 14 (7.1%) who had TEEs in the plasma group. The incidence of thromboembolic (TE) adverse reactions assessed as at least possibly related to study treatment by the Investigator or, in the case of serious thromboembolic events, the blinded safety adjudication board (SAB) was 9 (4.7%) in the KCENTRA group and 7 (3.6%) in the plasma group. When also considering the events which began during or within 72 hours of test product infusion, the incidence was 9 (4.7%) in the KCENTRA group and 8 (4.1%) in the plasma group.

TE events observed in the acute major bleeding and the urgent surgery/invasive procedures RCTs are shown in Table 4.

Table 4: Adverse Reactions (TEEs only) Following KCENTRA or Plasma Administration in RCTs
 | No. (%) of subjects
System Organ Class | Acute Major Bleeding Study |  | Urgent Surgery/Invasive Procedures Study
 | KCENTRA (N = 103) | Plasma (N = 109) | KCENTRA (N = 88) | Plasma (N = 88)
Any possible TEE [The tabulation of possible TEEs includes subjects with confirmed TEEs as well as 3 subjects in the Acute Major Bleeding RCT KCENTRA group that died of unknown causes on days 7, 31, and 38 and 1 subject in the Urgent Surgery/Invasive Procedures RCT plasma group that died of unknown causes on day 18. The death on day 7 was considered possibly related to study product by the SAB and is tabulated as an adverse reaction.] | 9 (8.7%) | 6 (5.5%) | 4 (4.5) | 8 (9.1)
TEE Adverse reactions | 6 (5.5%) | 4 (3.7%) | 4 (4.5) | 4 (4.5)
Cardiac disorders
Myocardial infarction | 0 | 1 (0.9%) | 0 | 2 (2.3)
Myocardial ischemia | 0 | 2 (1.8%) | 0 | 0
Nervous system disorders
Ischemic cerebrovascular accident (stroke) | 2 (1.9%) | 0 | 1 (1.1) | 0
Embolic cerebral infarction | 0 | 0 | 0 | 1 (1.1)
Cerebrovascular disorder | 0 | 1 (0.9%) | 0 | 0
Vascular disorders
Venous thrombosis calf | 1 (1.0%) | 0 | 0 | 0
Venous thrombosis radial vein | 0 | 0 | 1 (1.1) | 0
Thrombosis (microthrombosis of toes) | 0 | 0 | 1 (1.1) | 0
Deep vein thrombosis (DVT) | 1 (1.0%) | 0 | 1 (1.1) | 1 (1.1)
Fistula Clot | 1 (1.0%) | 0 | 0 | 0
Unknown Cause of Death (not confirmed TEE)
Sudden death | 1 (1.0%) | 0 | 0 | 0

Subgroup analyses of the RCTs according to whether subjects with thromboembolic events had a prior history of a thromboembolic event are presented in Table 5.

Table 5: Subjects with Thromboembolic Events by Prior History of TE Event in RCTs
 | Acute Major Bleeding Study |  |  |  | Urgent Surgery/Invasive Procedures Study
 | KCENTRA |  | Plasma |  | KCENTRA |  | Plasma
 | N | TE Events [One additional subject in the Acute Major Bleeding RCT who had received KCENTRA, not listed in the table, had an upper extremity venous thrombosis in association with an indwelling catheter. Two additional subjects in the Urgent Surgery/Invasive Procedures RCT who had received KCENTRA, not listed in the table, had non-intravascular events (catheter-related/IVC filter insertion).] N (%) | N | TE Events N (%) | N | TE Events N (%) | N | TE Events N (%)
All subjects | 103 | 9 (8.7) | 109 | 6 (5.5) | 88 | 4 (4.5) | 88 | 8 (9.1)
With history of TE event [History of prior TE event greater than 3 months from study entry (TE event within 3 months not studied).] | 69 | 8 (11.6) | 79 | 3 (3.8) | 55 | 3 (5.5) | 62 | 5 (8.1)
Without history of TE event | 34 | 1 (2.9) | 30 | 3 (10.0) | 33 | 1 (3.0) | 26 | 3 (11.5)

The European Bleeding and Surgical Study

In a prospective, open label, single-arm, multicenter safety and efficacy trial, 17 subjects who required urgent reversal of VKA due to acute bleeding were enrolled and 26 subjects who required urgent reversal of Vitamin K antagonist due to the need for an urgent surgical/invasive procedure were enrolled, all were treated with KCENTRA. Subjects ranged in age from 22 years to 85 years. Serious adverse reactions considered possibly related to KCENTRA included a suspected pulmonary embolism which occurred in one subject following a second dose of KCENTRA. A single non-fatal TE event occurred in another KCENTRA-treated subject in that trial.

6.2 Postmarketing Experience

In a postmarketing observational study, the risk of TEEs was assessed using Kaiser Permanente's databases in a matched, real-world cohort of hospitalized adults receiving either KCENTRA or plasma for VKA-associated major bleeding. For the primary analysis, 1119 KCENTRA patients and 1119 historical plasma patients with no recent history of TEEs were grouped in 1:1 individually matched cohort based on propensity scores. During the 45-day follow-up after acute VKA reversal, there was no statistically significant difference in the adjusted risk of TEEs between KCENTRA-treated patients and plasma-treated patients. . In a secondary analysis, 101 KCENTRA patients and 101 historical plasma patients with a recent history of TEEs diagnosed ≤90 days before study entry were also grouped in 1:1 individually matched cohort based on propensity scores. During the 45-day follow-up after acute VKA reversal, there was no statistically significant difference in the adjusted risk of TEEs between KCENTRA-treated patients and plasma-treated patients.

8 USE IN SPECIFIC POPULATIONS

8.1 Pregnancy

Risk Summary

There are no data with KCENTRA use in pregnancy to inform on drug-associated risk. Animal reproduction studies have not been conducted with KCENTRA. It is not known whether KCENTRA can cause fetal harm when administered to a pregnant woman or can affect reproduction capacity. KCENTRA should be prescribed for a pregnant woman only if clearly needed.

In the U.S. general population, the estimated background risk of major birth defect and miscarriage in clinically recognized pregnancies is 2-4% and 15-20%, respectively.

8.2 Lactation

Risk Summary

There is no information regarding the excretion of KCENTRA in human milk, the effect on the breastfed infant, or the effects on milk production. Because many drugs are excreted in human milk, use KCENTRA only if clearly needed when treating a nursing woman.

8.4 Pediatric Use

The safety and efficacy of KCENTRA in the pediatric population has not been studied.

8.5 Geriatric Use

Of the total number of subjects (431) with acute major bleeding or with the need for an urgent surgery/invasive procedure treated to reverse VKA anticoagulation in three clinical studies, 66% were 65 years old or greater and 39% were 75 years old or greater. There were no clinically significant differences between the safety profile of KCENTRA and plasma in any age group.

8.6 Congenital Factor Deficiencies

KCENTRA has not been studied in patients with congenital factor deficiencies.

11 DESCRIPTION

KCENTRA is a purified, heat-treated, nanofiltered and lyophilized non-activated four-factor Prothrombin Complex Concentrate (Human) prepared from human U.S. Source Plasma (21 CFR 640.60). It contains the Vitamin K dependent Coagulation Factors II, VII, IX and X, and the antithrombotic Proteins C and S. Factor IX is the lead factor for the potency of the preparation as stated on the vial label. The excipients are human antithrombin III, heparin, human albumin, sodium chloride, and sodium citrate. KCENTRA is sterile, pyrogen-free, and does not contain preservatives.

The product contents are shown in Table 6 and listed as ranges for the blood coagulation factors.

Table 6: Composition per Vial of KCENTRA [Exact potency of coagulant and antithrombotic proteins are listed on the carton]
Ingredient | Potency Range for 500 units | Potency Range for 1000 units
Total protein | 120–280 mg | 240–560 mg
Factor II | 380–800 units | 760–1600 units
Factor VII | 200–500 units | 400–1000 units
Factor IX | 400–620 units | 800–1240 units
Factor X | 500–1020 units | 1000–2040 units
Protein C | 420–820 units | 840–1640 units
Protein S | 240–680 units | 480–1360 units
Heparin | 8–40 units | 16–80 units
Antithrombin III | 4–30 units | 8–60 units
Human albumin | 40–80 mg | 80–160 mg
Sodium chloride | 60–120 mg | 120–240 mg
Sodium citrate | 40–80 mg | 80–160 mg
HCl | Small amounts | Small amounts
NaOH | Small amounts | Small amounts

All plasma used in the manufacture of KCENTRA is obtained from US donors and is tested using serological assays for hepatitis B surface antigen and antibodies to HIV-1/2 and HCV. The plasma is tested with Nucleic Acid Testing (NAT) for HCV, HIV-1, HAV, and HBV, and found to be non-reactive (negative), and the plasma is also tested by NAT for human parvovirus B19 (B19V) in order to exclude donations with high titers. The limit for B19V in the fractionation pool is set not to exceed 10^4 units of B19V DNA per mL. Only plasma that passed virus screening is used for production.

The KCENTRA manufacturing process includes various steps, which contribute towards the reduction/inactivation of viruses. KCENTRA is manufactured from cryo-depleted plasma that is adsorbed via ion exchange chromatography, heat treated in aqueous solution for 10 hours at 60°C, precipitated, adsorbed to calcium phosphate, virus filtered, and lyophilized.

Manufacturing steps were independently validated in a series of in vitro experiments for their virus inactivation / reduction capacity for both enveloped and non-enveloped viruses. Table 7 shows the virus clearance during the manufacturing process for KCENTRA, expressed as the mean log10 reduction factor.

Table 7: Mean Virus Reduction Factors [log10] of KCENTRA
Virus Studied | Manufacturing Steps
Virus Studied | Heat treatment ("Pasteurization") | Ammonium sulphate precipitation followed by Ca Phosphate adsorption | 2 × 20 nm Virus Filtration | Overall Virus Reduction [log10]
Enveloped Viruses
HIV | ≥ 5.9 | ≥ 5.9 | ≥ 6.6 | ≥ 18.4
BVDV | ≥ 8.5 | 2.2 | ≥ 6.0 | ≥ 16.7
PRV | 3.8 | 7.2 | ≥ 6.6 | ≥ 17.6
WNV | ≥ 7.4 | n.d. | ≥ 8.1 | ≥ 15.5
Non-Enveloped Viruses
HAV | 4.0 | 1.8 | ≥ 6.1 | ≥ 11.9
CPV | [0.5] [Reduction factor below 1 log10 was not considered in calculating the overall virus reduction. Studies using human parvovirus B19, which are considered experimental in nature, have demonstrated a virus reduction factor of 3.5 log10 by heat treatment.] | 1.5 | 6.5 | 8.0
HIV Human immunodeficiency virus, a model for HIV-1 and HIV-2
BVDV Bovine viral diarrhea virus, model for HCV
PRV Pseudorabies virus, a model for large enveloped DNA viruses
WNV West Nile virus
HAV Hepatitis A virus
CPV Canine parvovirus, model for B19V
n.d. not determined

12 CLINICAL PHARMACOLOGY

12.1 Mechanism of Action

KCENTRA contains the Vitamin K-dependent coagulation Factors II (FII), VII (FVII), IX (FIX), and X (FX), together known as the Prothrombin Complex, and the antithrombotic Protein C and Protein S.

A dose-dependent acquired deficiency of the Vitamin K-dependent coagulation factors occurs during Vitamin K antagonist treatment. Vitamin K antagonists exert anticoagulant effects by blocking carboxylation of glutamic acid residues of the Vitamin K-dependent coagulation factors during hepatic synthesis, lowering both factor synthesis and function. The administration of KCENTRA rapidly increases plasma levels of the Vitamin K-dependent coagulation Factors II, VII, IX, and X as well as the antithrombotic Proteins C and S.

Coagulation Factor II

Factor II (prothrombin) is converted to thrombin by activated FX (FXa) in the presence of Ca^2+, FV, and phospholipids.

Coagulation Factor VII

Factor VII (proconvertin) is converted to the activated form (FVIIa) by splitting of an internal peptide link. The FVIIa-TF complex activates Factor IX and initiates the primary coagulation pathway by activating FX in the presence of phospholipids and calcium ions.

Coagulation Factor IX

Factor IX (antihemophilic globulin B, or Christmas factor) is activated by the FVIIa-TF complex and by FXIa. Factor IXa in the presence of FVIIIa activates FX to FXa.

Coagulation Factor X

Factor X (Stuart-Prower factor) activation involves the cleavage of a peptide bond by the FVIIIa-Factor IXa complex or the TF-FVIIa complex. Factor Xa forms a complex with activated FV (FVa) that converts prothrombin to thrombin in the presence of phospholipids and calcium ions.

Protein C

Protein C, when activated by thrombin, exerts an antithrombotic effect by inhibiting FVa and FVIIIa leading to a decrease in thrombin formation, and has indirect profibrinolytic activity by inhibiting plasminogen activator inhibitor-1.

Protein S

Protein S exists in a free form (40%) and in a complex with C4b-binding protein (60%). Protein S (free form) functions as a cofactor for activated Protein C in the inactivation of FVa and FVIIIa, leading to antithrombotic activity.

12.2 Pharmacodynamics

International Normalized Ratio (INR)

In the plasma-controlled RCT in acute major bleeding, the INR was determined at varying time points after the start or end of infusion, depending upon study design. The median INR was above 3.0 prior to the infusion and dropped to a median value of 1.20 by the 30 minute time point after start of KCENTRA infusion. By contrast, the median value for plasma was 2.4 at 30 minutes after the start of infusion. The INR differences between KCENTRA and plasma were statistically significant in randomized plasma-controlled trial in bleeding up to 12 hours after start of infusion [see Table 8].

The relationship between these or other INR values and clinical hemostasis in patients has not been established [see Clinical Studies (14)].

Table 8: Median INR (Min-Max) after Start of Infusion in RCTs
Study | Treatment | Baseline | 30 min | 1 hr | 2-3 hr | 6-8 hr | 12 hr | 24 hr
Acute Major Bleeding Study | KCENTRA (N = 98) | 3.90 (1.8–20.0) | 1.20 [Statistically significant difference compared to plasma by 2-sided Wilcoxon test] (0.9–6.7) | 1.30 (0.9–5.4) | 1.30 (0.9–2.5) | 1.30 (0.9–2.1) | 1.20 (0.9–2.2) | 1.20 (0.9–3.8)
Acute Major Bleeding Study | Plasma (N = 104) | 3.60 (1.9–38.9) | 2.4 (1.4–11.4) | 2.1 (1.0–11.4) | 1.7 (1.1–4.1) | 1.5 (1.0–3.0) | 1.4 (1.0–3.0) | 1.3 (1.0–2.9)
Urgent Surgery/ Invasive Procedures Study | KCENTRA (N = 87) | 2.90 (2.0–17.0) | 1.30 (0.9–7.0) | 1.20 (0.9–2.5) | 1.30 (0.9–39.2) | 1.30 (1.0–10.3) | NC | 1.20 (0.9–2.7)
Urgent Surgery/ Invasive Procedures Study | Plasma (N = 81) | 2.90 (2.0–26.7) | 2.15 (1.4–5.4) | 1.90 (1.3–5.7) | 1.70 (1.1–3.7) | 1.60 (1.0–5.8) | NC | 1.30 (1.0–2.7)
INR = international normalized ratio; NC = not collected.

12.3 Pharmacokinetics

Fifteen healthy subjects received 50 units/kg of KCENTRA. No subjects were receiving VKA therapy or were experiencing acute bleeding. A single intravenous KCENTRA infusion produced a rapid and sustained increase in plasma concentration of Factors II, VII, IX and X as well as Proteins C and S. The PK analysis [see Table 9] shows that factor II had the longest half-life (59.7 hours) and factor VII the shortest (4.2 hours) in healthy subjects. PK parameters obtained from data derived from the study of healthy subjects may not be directly applicable to patients with INR elevation due to VKA anticoagulation therapy.

Table 9: Vitamin K-Dependent Coagulation Factor Pharmacokinetics after a Single KCENTRA Infusion in Healthy Subjects (n=15) Mean (SD) [IVR: In Vivo Recovery]
Parameter | Factor IX | Factor II | Factor VII | Factor X | Protein C | Protein S
Terminal half-life (h) | 42.4 (41.6) | 60.4 (25.5) | 5.0 (1.9) | 31.8 (8.7) | 49.6 (32.7) | 50.4 (13.4)
IVR (%/units/kg bw) | 1.6 (0.4) | 2.2 (0.3) | 2.5 (0.4) | 2.2 (0.4) | 2.9 (0.3) | 2.0 (0.3)
AUC (IU/dL × h) | 1850.8 (1001.4) | 7282.2 (2324.9) | 512.9 (250.1) | 6921.5 (1730.5) | 5397.5 (2613.9) | 3651.6 (916.3)
Clearance (mL/ kg × h) | 3.7 (1.6) | 1.0 (0.3) | 7.4 (4.1) | 1.3 (0.3) | 1.5 (0.9) | 1.2 (0.3)
MRT (h) [MRT: Mean Residence Time] | 47.3 (49.5) | 82.0 (34.2) | 7.1 (2.7) | 45.9 (12.6) | 62.4 (42.1) | 70.3 (18.3)
Vdss (mL/kg) [Vdss: Volume of Distribution at steady state] | 114.3 (54.6) | 71.4 (13.7) | 45.0 (10.7) | 55.5 (6.7) | 62.2 (17.4) | 78.8 (11.6)

The mean in vivo recovery (IVR) of infused factors was calculated in subjects who received KCENTRA. The IVR is the increase in measurable factor levels in plasma (units/dL) that may be expected following an infusion of factors (units/kg) administered as a dose of KCENTRA. The in vivo recovery ranged from 1.15 (Factor IX) to 2.81 (Protein S) [see Table 10].

Table 10: In vivo Recovery in RCTs [ITT-E: Intention to Treat – Efficacy Population]
Parameter | Incremental (units/dL per units/kg b.w.)
Parameter | Acute Major Bleeding Study (N = 98) |  | Urgent Surgery/Invasive Procedures Study (N = 87)
Parameter | Mean (SD) | 95% CI [CI: Confidence Interval] | Mean (SD) | 95% CI
Factor IX | 1.29 (0.71) | (1.14–1.43) | 1.15 (0.57) | (1.03–1.28)
Factor II | 2.00 (0.88) | (1.82–2.18) | 2.14 (0.74) | (1.98–2.31)
Factor VII | 2.15 (2.96) | (1.55–2.75) | 1.90 (4.50) | (0.92–2.88)
Factor X | 1.96 (0.87) | (1.79–2.14) | 1.94 (0.69) | (1.79–2.09)
Protein C | 2.04 (0.96) | (1.85–2.23) | 1.88 (0.68) | (1.73–2.02)
Protein S | 2.17 (1.66) | (1.83–2.50) | 2.81 (1.95) | (2.38–3.23)

13 NONCLINICAL TOXICOLOGY

13.1 Carcinogenesis, Mutagenesis, Impairment of Fertility

Long-term studies in animals to evaluate the carcinogenic potential of KCENTRA, or studies to determine the effects of KCENTRA on genotoxicity or fertility have not been performed. An assessment of the carcinogenic potential of KCENTRA was completed and suggests minimal carcinogenic risk from product use.

14 CLINICAL STUDIES

Acute Major Bleeding RCT

The efficacy of KCENTRA has been evaluated in a prospective, open-label, (blinded assessor), active-controlled, non-inferiority, multicenter RCT in subjects who had been treated with VKA therapy and who required urgent replacement of their Vitamin K-dependent clotting factors to treat acute major bleeding. A total of 216 subjects with acquired coagulation factor deficiency due to oral Vitamin K antagonist therapy were randomized to a single dose of KCENTRA or plasma. Two hundred twelve (212) subjects received KCENTRA or plasma for acute major bleeding in the setting of a baseline INR ≥ 2.0 and recent use of a VKA anticoagulant. The doses of KCENTRA (25 units/kg, 35 units/kg, or 50 units/kg) based on nominal Factor IX content and plasma (10 mL/kg, 12 mL/kg, or 15 mL/kg) were calculated according to the subject's baseline INR (2–< 4, 4–6, > 6, respectively). The observation period lasted for 90 days after the infusion of KCENTRA or plasma. The modified efficacy (ITT-E) population for KCENTRA included 98 subjects and for plasma included 104 subjects. Additionally, intravenous Vitamin K was administered.

The efficacy endpoint was hemostatic efficacy for the time period from the start of infusion of KCENTRA or plasma until 24 hours. Efficacy was adjudicated as "effective" or "not effective" by a blinded, independent Endpoint Adjudication Board for all subjects who received study product. Criteria for effective hemostasis were based upon standard clinical assessments including vital signs, hemoglobin measurements, and CT assessments at pre-defined time points, as relevant to the type of bleeding (i.e., gastrointestinal, intracranial hemorrhage, visible, musculoskeletal, etc.). The proportion of subjects with effective hemostasis was 72.4% in the KCENTRA group and 65.4% in the plasma group. The lower limit of the 95% confidence interval (CI) for the difference in proportions of KCENTRA minus plasma was -5.8%, which exceeded -10% and thereby demonstrated the non-inferiority of KCENTRA versus plasma (the study's primary objective) [see Table 11]. Because the lower limit of the CI was not greater than zero, the prospectively defined criterion for superiority of KCENTRA for hemostatic efficacy (a secondary objective) was not met.

Table 11: Rating of Hemostatic Efficacy in Subjects with Acute Major Bleeding
Rating | No. (%) of subjects [95% CI] |  | Difference KCENTRA – Plasma (%) [95% CI] [KCENTRA non-inferior to plasma if lower limit of 95% CI > –10%; KCENTRA superior to plasma if lower limit of 95% CI > 0.]
Rating | KCENTRA (N = 98) | Plasma (N = 104) | Difference KCENTRA – Plasma (%) [95% CI] [KCENTRA non-inferior to plasma if lower limit of 95% CI > –10%; KCENTRA superior to plasma if lower limit of 95% CI > 0.]
"Effective" hemostasis | 71 (72.4%) [62.3; 82.6] | 68 (65.4%) [54.9; 75.8] | (7.1%) [-5.8; 19.9]
CI = confidence interval; N = number of subjects

Results of a post-hoc analysis of hemostatic efficacy stratified by actual dose of KCENTRA or plasma administered in the acute major bleeding RCT are presented in Table 12.

Table 12: Rating of Hemostatic Efficacy Stratified by Actual Dose of KCENTRA or Plasma (Number and % of Subjects rated "Effective") in Acute Major Bleeding RCT
 | Low Dose | Mid Dose | High Dose
 | N = 49 (K) | N = 22 (K) | N = 26 (K)
 | N = 55 (P) | N = 18 (P) | N = 31 (P)
KCENTRA | 36 (74.5%) | 16 (72.7%) | 18 (69.2%)
Plasma | 38 (69.1%) | 11 (61.1%) | 19 (61.3%)
Difference [KCENTRA minus Plasma] | (4.4%) | (11.6%) | (7.9%)
95% CI K–P | -13.2–21.9 | -17.4–40.6 | -17.0–32.9

An additional endpoint was the reduction of INR to ≤ 1.3 at 30 minutes after the end of infusion of KCENTRA or plasma for all subjects that received study product. The proportion of subjects with this decrease in INR was 62.2% in the KCENTRA group and 9.6% in the plasma group. The 95% confidence interval for the difference in proportions of KCENTRA minus plasma was 39.4% to 65.9%. The lower limit of the 95% CI of 39.4% demonstrated superiority of KCENTRA versus plasma for this endpoint [see Table 13].

Table 13: Decrease of INR (1.3 or Less at 30 Minutes after End of Infusion) in Acute Major Bleeding RCT
Rating | No. (%) of subjects [95% CI] |  | Difference KCENTRA – Plasma (%) [95% CI] [KCENTRA non-inferior to plasma if lower limit of 95% CI > –10%; KCENTRA superior to plasma if lower limit of 95% CI > 0.]
Rating | KCENTRA (N = 98) | Plasma (N = 104) | Difference KCENTRA – Plasma (%) [95% CI] [KCENTRA non-inferior to plasma if lower limit of 95% CI > –10%; KCENTRA superior to plasma if lower limit of 95% CI > 0.]
Decrease of INR to ≤ 1.3 at 30 min | 61 (62.2%) [52.6; 71.8] | 10 (9.6%) [3.9; 15.3] | (52.6%) [39.4; 65.9]
CI = confidence interval; INR = international normalized ratio; N = total subjects

Urgent Surgery/Invasive Procedure RCT

The efficacy of KCENTRA has been evaluated in a prospective, open-label, active-controlled, non-inferiority, multicenter RCT in subjects who had been treated with VKA therapy and who required urgent replacement of their Vitamin K-dependent clotting factors because of their need for an urgent surgery/invasive procedure. A total of 181 subjects with acquired coagulation factor deficiency due to oral Vitamin K antagonist therapy were randomized to a single dose of KCENTRA or plasma. One hundred seventy-six (176) subjects received KCENTRA or plasma because of their need for an urgent surgery/invasive procedure in the setting of a baseline INR ≥ 2.0 and recent use of a VKA anticoagulant. The doses of KCENTRA (25 units/kg, 35 units/kg, or 50 units/kg) based on nominal Factor IX content and plasma (10 mL/kg, 12 mL/kg, or 15 mL/kg) were calculated according to the subject's baseline INR (2–< 4, 4–6, > 6, respectively). The observation period lasted for 90 days after the infusion of KCENTRA or plasma. The modified efficacy (ITT-E) population for KCENTRA included 87 subjects and for plasma included 81 subjects. Additionally, oral or intravenous Vitamin K was administered.

The efficacy endpoint was hemostatic efficacy for the time period from the start of infusion of KCENTRA or plasma until the end of the urgent surgery/invasive procedure. Criteria for effective hemostasis were based upon the difference between predicted and actual blood losses, subjective hemostasis rating, and the need for additional blood products containing coagulation factors. The proportion of subjects with effective hemostasis was 89.7% in the KCENTRA group and 75.3% in the plasma group. The lower limit of the 95% confidence interval (CI) for the difference in proportions of KCENTRA minus plasma was 2.8%, which exceeded -10% and thereby demonstrated the non-inferiority of KCENTRA versus plasma (the study's primary objective) [see Table 14]. Because the lower limit of the CI was greater than 0, the prospectively defined criterion for superiority of KCENTRA for hemostatic efficacy (a secondary objective) was also met.

Table 14: Rating of Hemostatic Efficacy in Urgent Surgery/Invasive Procedure RCT
Rating | No. (%) of subjects [95% CI] |  | Difference KCENTRA – Plasma (%) [95% CI] [KCENTRA non-inferior to plasma if lower limit of 95% CI > –10%; KCENTRA superior to plasma if lower limit of 95% CI > 0.]
Rating | KCENTRA (N = 87) | Plasma (N = 81) | Difference KCENTRA – Plasma (%) [95% CI] [KCENTRA non-inferior to plasma if lower limit of 95% CI > –10%; KCENTRA superior to plasma if lower limit of 95% CI > 0.]
"Effective" hemostasis | 78 (89.7%) [83.3; 96.1] | 61 (75.3%) [65.9; 84.7] | (14.3%) [2.8; 25.8]
CI = confidence interval; N = number of subjects

Results of a post-hoc analysis of hemostatic efficacy stratified by actual dose of KCENTRA or plasma administered in the urgent surgery/invasive procedure RCT are presented in Table 15.

Table 15: Rating of Hemostatic Efficacy Stratified by Actual Dose of KCENTRA or Plasma (Number and % of Subjects rated "Effective") in Urgent Surgery/Invasive Procedure RCT
 | Low Dose | Mid Dose | High Dose
 | N = 69 (K) | N = 10 (K) | N = 8 (K)
 | N = 62 (P) | N = 10 (P) | N = 9 (P)
KCENTRA | 63 (91.3%) | 8 (80.0%) | 7 (87.5%)
Plasma | 48 (77.4%) | 7 (70.0%) | 6 (66.7%)
Difference [KCENTRA minus Plasma] | (13.9%) | (10.0%) | (20.8%)
95% CI K–P | 1.4–26.6 | -26.5–43.5 | -19.8–53.7

An additional endpoint was the reduction of INR to ≤ 1.3 at 30 minutes after the end of infusion of KCENTRA or plasma for all subjects that received study product. The proportion of subjects with this decrease in INR was 55.2% in the KCENTRA group and 9.9% in the plasma group. The 95% confidence interval for the difference in proportions of KCENTRA minus plasma was 31.9% to 56.4%. The lower limit of the 95% CI of 31.9% demonstrated superiority of KCENTRA versus plasma for this endpoint [see Table 16]. The relationship between a decrease in INR to less than or equal to 1.3 and clinical hemostatic efficacy has not been established.

Table 16: Decrease of INR (1.3 or Less at 30 Minutes after End of Infusion) in Urgent Surgery/Invasive Procedure RCT
Rating | No. (%) of subjects [95% CI] |  | Difference KCENTRA – Plasma (%) [95% CI] [KCENTRA non-inferior to plasma if lower limit of 95% CI > -10%; KCENTRA superior to plasma if lower limit of 95% CI > 0.]
Rating | KCENTRA (N = 87) | Plasma (N = 81) | Difference KCENTRA – Plasma (%) [95% CI] [KCENTRA non-inferior to plasma if lower limit of 95% CI > -10%; KCENTRA superior to plasma if lower limit of 95% CI > 0.]
Decrease of INR to ≤ 1.3 at 30 min | 48 (55.2%) [44.7; 65.6] | 8 (9.9%) [3.4; 16.4] | (45.3%) [31.9; 56.4]
CI = confidence interval; INR = international normalized ratio; N = total subjects

The European Bleeding and Surgical Study was an open-label, single-arm, multicenter study.^1 Forty-three (43) subjects who were receiving VKA were treated with KCENTRA, because they either (1) required a surgical or an invasive diagnostic intervention (26 subjects), or (2) experienced an acute bleeding event (17 subjects). The dose of KCENTRA (25 units/kg, 35 units/kg, or 50 units/kg) based on nominal Factor IX content was calculated according to the subject's baseline INR value (2–< 4, 4–6, > 6). The endpoint was the decrease of the INR to ≤ 1.3 within 30 minutes after end of KCENTRA infusion in subjects who received any portion of study product.

Of the 17 evaluable subjects receiving KCENTRA for acute bleeding, 16 subjects (94%) experienced a decrease in INR to ≤ 1.3 within 30 minutes after the end of the KCENTRA infusion.

In RCTs, levels of Coagulation Factors II, VII, IX, X, and Antithrombotic Proteins C and S were measured after the infusion of KCENTRA or plasma and the results were similar for subjects with acute major bleeding or subjects requiring an urgent surgery or invasive procedure. In the plasma-controlled RCT in acute major bleeding, the mean duration of KCENTRA infusion was 24 minutes (± 32 minutes) and the mean duration of infusion for plasma was 169 minutes (± 143 minutes). The mean infusion volume of KCENTRA was 105 mL ± 37 mL and the mean infusion volume of plasma was 865 mL ± 269 mL. In the plasma-controlled RCT for patients needing urgent surgery/invasive procedures, the mean duration of KCENTRA infusion was 21 minutes (± 14 minutes) and the mean duration of infusion for plasma was 141 minutes (± 113 minutes). The mean infusion volume of KCENTRA was 90 mL ± 32 mL and the mean infusion volume of plasma was 819 mL ± 231 mL.

The increase in mean factor levels over time following KCENTRA and plasma administration in the plasma-controlled RCT in acute major bleeding is shown in Figure 9 below (the mean factor levels over time following KCENTRA and plasma administration in the plasma-controlled RCT for patients needing urgent surgery/invasive procedures are not shown, but showed similar profiles). Levels of some factors continued to increase at later time points, consistent with the effect of concomitant Vitamin K treatment. Formal pharmacokinetic parameters were not derived because of the effect of Vitamin K on factor levels at time points required for pharmacokinetic profiling.

Figure 9: Mean Factor Levels (Factors II, VII, IX, X, Proteins C & S) over 24 hours in Acute Major Bleeding RCT

Time axis is scheduled measuring time: hours after start of infusion (P=pre-infusion)

15 REFERENCES

1. Pabinger I, Brenner B, Kalina U, et al. Prothrombin complex concentrate (Beriplex P/N) for emergency anticoagulation reversal: a prospective multinational clinical trial. Journal of Thrombosis and Haemostasis 2008; 6: 622-631.

16 HOW SUPPLIED/STORAGE AND HANDLING

- KCENTRA is supplied in a single-dose vial.
- The actual units of potency of all coagulation factors (Factors II, VII, IX and X), Proteins C and S in units are stated on each KCENTRA carton.
- The KCENTRA packaging components are not made with natural rubber latex.

Table 17. How Supplied

Each kit consists of the following:

Carton NDC Number | Components
63833-386-02 | - Nominal potency 500 (range 400-620) units KCENTRA in a single-dose vial [NDC 63833-396-01] - 20 mL vial of Sterile Water for Injection, USP [NDC 63833-761-20] - Mix2Vial filter transfer set - Alcohol swab
63833-387-02 | - Nominal potency 1000 (range 800-1240) units KCENTRA in a single-dose vial [NDC 63833-397-01] - 40 mL vial of Sterile Water for Injection, USP [NDC 63833-761-40] - Mix2Vial filter transfer set - Alcohol swab

Storage and Handling

Prior to Reconstitution

- KCENTRA is for single-dose only. Contains no preservatives.
- Store KCENTRA between 2–25°C (36–77°F), this includes room temperature, not to exceed 25°C (77°F). Do not freeze.
- KCENTRA is stable for 36 months from the date of manufacture, up to the expiration date on the carton and vial labels.
- Do not use KCENTRA beyond the expiration date on the vial label and carton.
- Store the vial in the original carton to protect it from light.

After Reconstitution

KCENTRA must be used within 4 hours following reconstitution. Reconstituted KCENTRA can be stored at 2–25°C. If cooled, the solution should be warmed to 20–25°C prior to administration. Do not freeze. Discard partially used vials.

17 PATIENT COUNSELING INFORMATION

- Inform patients of the signs and symptoms of allergic hypersensitivity reactions, such as urticaria, rash, tightness of the chest, wheezing, hypotension and/or anaphylaxis experienced during or after injection of KCENTRA [see Warnings and Precautions (5.1)].
- Inform patients of signs and symptoms of thrombosis, such as limb or abdomen swelling and/or pain, chest pain or pressure, shortness of breath, loss of sensation or motor power, altered consciousness, vision, or speech [see Warnings and Precautions (5.2)].
- Inform patients that, because KCENTRA is made from human blood, it may carry a risk of transmitting infectious agents, e.g., viruses, the variant Creutzfeldt-Jakob disease (vCJD) agent, and theoretically, the Creutzfeldt-Jakob disease (CJD) agent [see Warnings and Precautions (5.3) and Description (11)].

Manufactured by:
CSL Behring GmbH
35041 Marburg Germany
US License No. 1765

Distributed by:
CSL Behring LLC
Kankakee, IL 60901 USA

Mix2Vial® is a registered trademark of West Pharma. Services IL, Ltd., a subsidiary of West Pharmaceuticals Services, Inc.

PRINCIPAL DISPLAY PANEL - Kit Carton - 500 U

NDC 63833-386-02

500 U Range

Prothrombin Complex
Concentrate (Human)
Kcentra®

One single-dose vial containing 400 – 620 units of lyophilized Factor IX concentrate for
reconstitution. Also contains Factors II, VII, X and proteins C and S.

For Intravenous Administration Only

Because Kcentra® is made from human blood, it may carry a risk of transmitting
infectious agents, e.g., viruses, the variant Creutzfeldt-Jakob disease (vCJD) agent,
and, theoretically, the Creutzfeldt-Jakob disease (CJD) agent.
See package insert Warnings and Precautions section.

CSL Behring

PRINCIPAL DISPLAY PANEL - Kit Carton - 1000 U

NDC 63833-387-02

1000 U Range

Prothrombin Complex
Concentrate (Human)
Kcentra®

One single-dose vial containing 800 – 1240 units
of lyophilized Factor IX concentrate for reconstitution.
Also contains Factors II, VII, X and proteins C and S.

For Intravenous Administration Only

Because Kcentra® is made from human blood, it may carry a risk of
transmitting infectious agents, e.g., viruses, the variant Creutzfeldt-Jakob
disease (vCJD) agent, and, theoretically, the Creutzfeldt-Jakob disease
(CJD) agent. See package insert Warnings and Precautions section.

CSL Behring